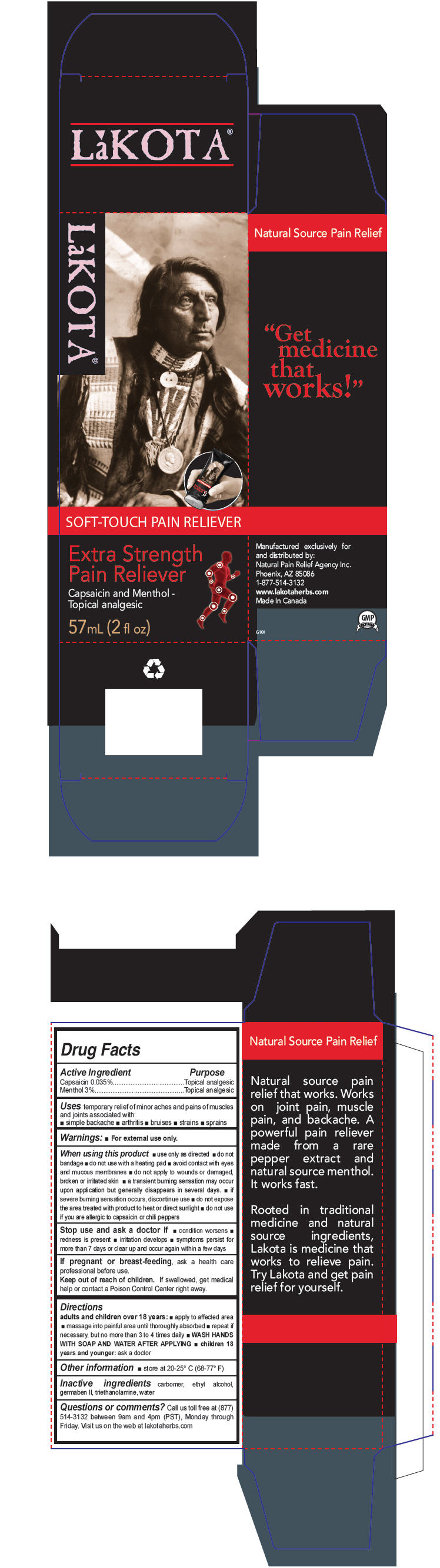 DRUG LABEL: Extra Strength Pain Reliever
NDC: 59092-002 | Form: CREAM
Manufacturer: HPI Health Products Inc.
Category: otc | Type: HUMAN OTC DRUG LABEL
Date: 20141030

ACTIVE INGREDIENTS: capsaicin 0.35 mg/1 mL; menthol, unspecified form 30 mg/1 mL
INACTIVE INGREDIENTS: carbomer interpolymer type A (allyl sucrose crosslinked); alcohol; diazolidinyl urea; trolamine; water

Extra Strength Pain Reliever

Drug Facts

ACTIVE INGREDIENT

Active Ingredient | Purpose
Capsaicin 0.035% | Topical analgesic
Menthol 3% | Topical analgesic

Uses

temporary relief of minor aches and pains of muscles and joints associated with:

- simple backache
- arthritis
- bruises
- strains
- sprains

Warnings

- For external use only.

When using this product

- use only as directed
- do not bandage
- do not use with a heating pad
- avoid contact with eyes and mucous membranes
- do not apply to wounds or damaged, broken or irritated skin
- a transient burning sensation may occur upon application but generally disappears in several days.
- if severe burning sensation occurs, discontinue use
- do not expose the area treated with product to heat or direct sunlight
- do not use if you are allergic to capsaicin or chili peppers

Stop use and ask a doctor if

- condition worsens
- redness is present
- irritation develops
- symptoms persist for more than 7 days or clear up and occur again within a few days

PREGNANCY OR BREAST FEEDING

If pregnant or breast-feeding, ask a health care professional before use.

Keep out of reach of children. If swallowed, get medical help or contact a Poison Control Center right away.

Directions

adults and children over 18 years:

- apply to affected area
- massage into painful area until thoroughly absorbed
- repeat if necessary, but no more than 3 to 4 times daily
- WASH HANDS WITH SOAP AND WATER AFTER APPLYING
- children 18 years and younger: ask a doctor

Other information

- store at 20-25° C (68-77° F)

Inactive ingredients

carbomer, ethyl alcohol, germaben II, triethanolamine, water

Questions or comments?

Call us toll free at (877) 514-3132 between 9am and 4pm (PST), Monday through Friday. Visit us on the web at lakotaherbs.com

Manufactured exclusively for
and distributed by:
Natural Pain Relief Agency Inc.
Phoenix, AZ 85086

PRINCIPAL DISPLAY PANEL - 57 mL Bottle Box

LaKOTA®

SOFT-TOUCH PAIN RELIEVER

Extra Strength
Pain Reliever

Capsaicin and Menthol -
Topical analgesic

57mL (2 fl oz)